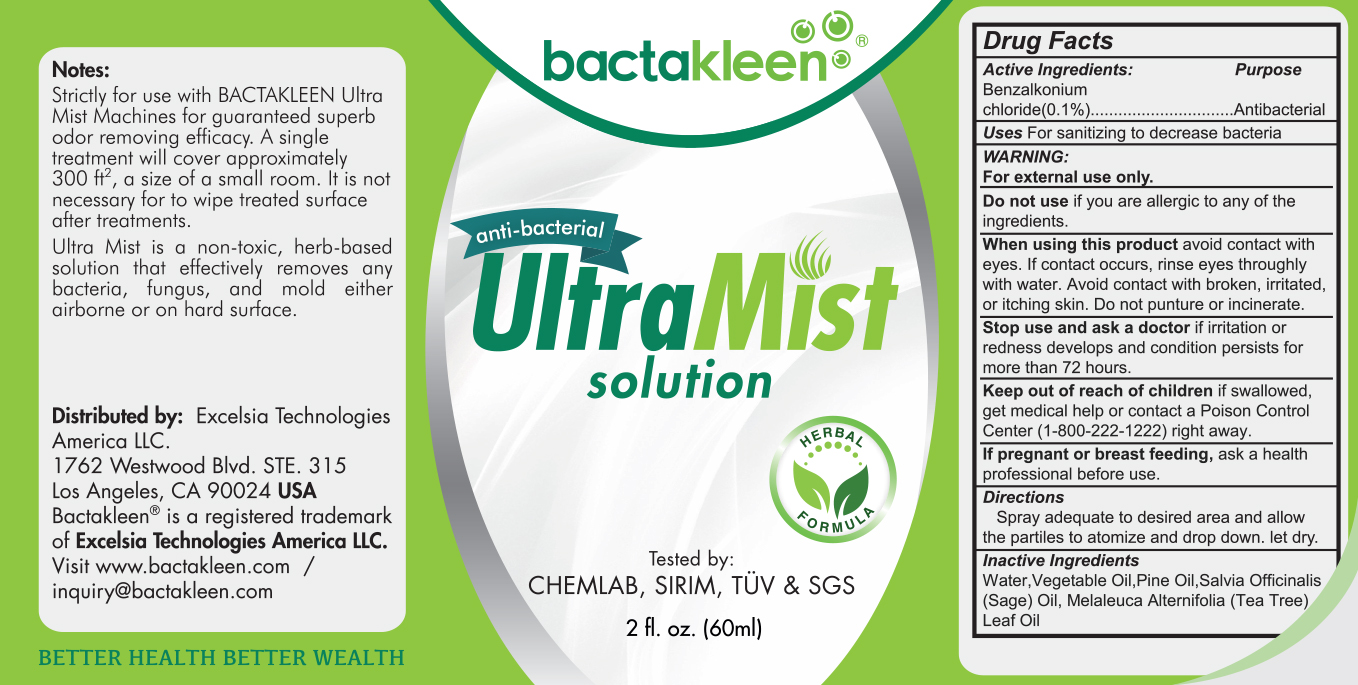 DRUG LABEL: Bactakleen Ultra Mist (60ml)
NDC: 73215-108 | Form: LIQUID
Manufacturer: Excelsia Technologies Sdn Bhd
Category: otc | Type: HUMAN OTC DRUG LABEL
Date: 20200321

ACTIVE INGREDIENTS: BENZALKONIUM CHLORIDE 0.06 g/60 mL
INACTIVE INGREDIENTS: WATER; SAGE OIL; TEA TREE OIL; WHITE PINE OIL

Bactakleen Ultra Mist (60ml)

Active Ingredients

Benzalkonium chloride (0.1%)

Purpose

Antibacterial

Keep out of reach of children

If swallowed, get medical help or contact a Poison Control Center (1-800-222-1222) right away.

Uses

For sanitizing to decrease bacteria

Warnings

For external use only

Do not use if you are allergic to any of the ingredients

When using this product avoid contact with eyes. If contact occurs, rinse eyes thoroughly with water. avoid contact with broken, irritated, or itching skin. Do not puncture or incinerate.

Stop use and ask a doctor if irritation or redness develops and condition persists for more than 72 hours

If pregnant or breast-feeding, ask a health professional before use.

Directions

Spray adequate amount to desired area.

Inactive Ingredients

Distilled water, Vegetable Oil, Pine Oil, Salvia Officinalis (Sage) Oil, Melaleuca Alternifolia (Tea Tree) Leaf Oil